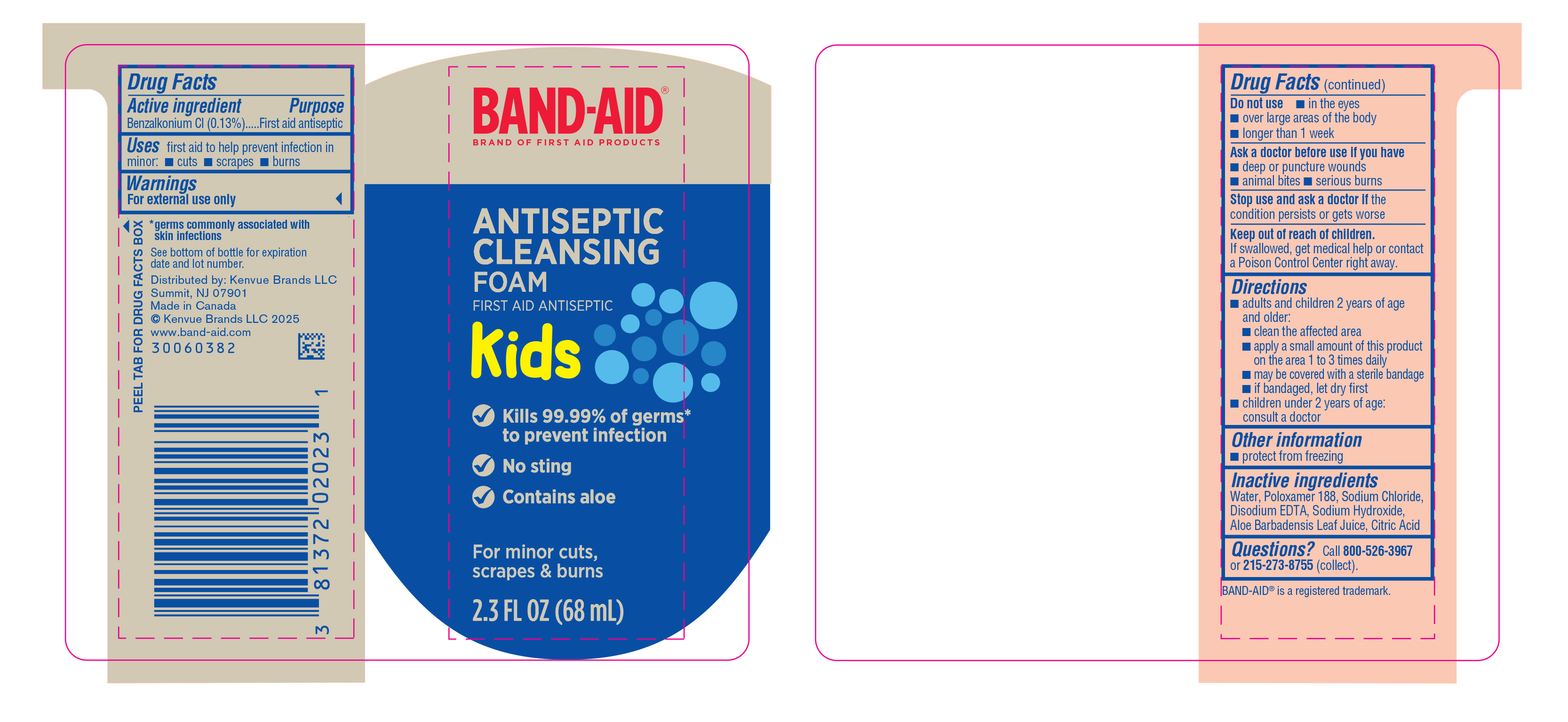 DRUG LABEL: Band Aid Antiseptic Cleansing
NDC: 69968-0728 | Form: AEROSOL, FOAM
Manufacturer: Kenvue Brands LLC
Category: otc | Type: HUMAN OTC DRUG LABEL
Date: 20250408

ACTIVE INGREDIENTS: BENZALKONIUM CHLORIDE 1.3 mg/1 mL
INACTIVE INGREDIENTS: WATER; POLOXAMER 188; EDETATE DISODIUM; SODIUM CHLORIDE; ALOE VERA LEAF; SODIUM HYDROXIDE; CITRIC ACID MONOHYDRATE

Band Aid Antiseptic Cleansing

Drug Facts

Active ingredient

Benzalkonium Cl (0.13%)

Purposes

First aid antiseptic

Use

first aid to help prevent infection in minor: · cuts · scrapes · burns

Warnings

- For external use only.

Do not use · in the eyes · over large area of the body · longer than 1 week

- Ask a doctor before use if you have · deep or puncture wounds · animal bites · serious burns

- Stop use and ask a doctor if the condition persists or gets worse

Keep out of reach of children.

If swallowed, get medical help or contact a Poison Control Center right away.

Directions

adults and children 2 years of age and older:

clean the affected area
apply a small amount of this product on the area 1 to 3 times daily
may be covered with a sterile bandage
if bandaged, let dry first

children under 2 years of age: consult a doctor

Other information

protect from freezing

Inactive ingredients

Water, Poloxamer 188, Sodium Chloride, Disodium EDTA, Sodium Hydroxide, Aloe Barbadensis Leaf Juice, Citric Acid

Questions?

call 800-526-3967 or 215-273-8755 (collect).

Distributed by:
Kenvue Brands LLC
Summit, NJ 07901

PRINCIPAL DISPLAY PANEL - 68 mL Bottle

BAND-AID®

BRAND OF FIRST AID PRODUCTS

ANTISEPTIC

CLEANISING

FOAM

FIRST AID ANTIBIOTIC

Kids

Kills 99.99% of germs*

to prevent infection

No sting

Contains aloe

For minor cuts,

scrapes & burns

2.3 FL OZ (68mL)